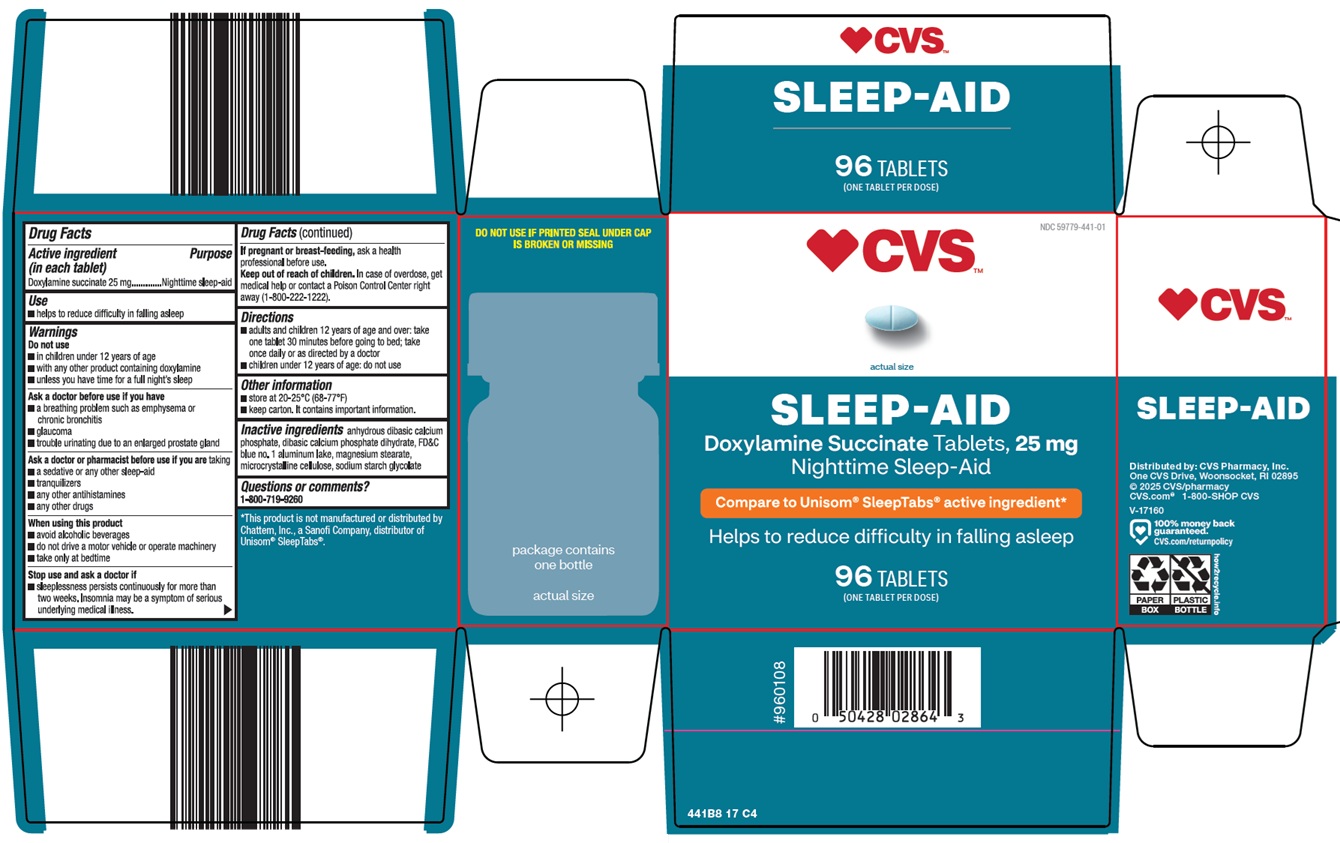 DRUG LABEL: NIGHTTIME SLEEP AID
NDC: 59779-441 | Form: TABLET
Manufacturer: CVS Pharmacy
Category: otc | Type: HUMAN OTC DRUG LABEL
Date: 20260227

ACTIVE INGREDIENTS: DOXYLAMINE SUCCINATE 25 mg/1 1
INACTIVE INGREDIENTS: ANHYDROUS DIBASIC CALCIUM PHOSPHATE; DIBASIC CALCIUM PHOSPHATE DIHYDRATE; FD&C BLUE NO. 1 ALUMINUM LAKE; MAGNESIUM STEARATE; MICROCRYSTALLINE CELLULOSE; SODIUM STARCH GLYCOLATE TYPE A

CVS Pharmacy, Inc. Sleep-Aid Drug Facts

Active ingredient (in each tablet)

Doxylamine succinate 25 mg

Purpose

Nighttime sleep-aid

Use

1. helps to reduce difficulty in falling asleep

Warnings

Do not use

- in children under 12 years of age
- with any other product containing doxylamine
- unless you have time for a full night’s sleep

Ask a doctor before use if you have

- a breathing problem such as emphysema or chronic bronchitis
- glaucoma
- trouble urinating due to an enlarged prostate gland

Ask a doctor or pharmacist before use if you are

taking

- a sedative or any other sleep-aid
- tranquilizers
- any other antihistamines
- any other drugs

When using this product

1. avoid alcoholic beverages
2. do not drive a motor vehicle or operate machinery
3. take only at bedtime

Stop use and ask a doctor if

1. sleeplessness persists continuously for more than two weeks. Insomnia may be a symptom of serious underlying medical illness.

If pregnant or breast-feeding,

ask a health professional before use.

Keep out of reach of children.

In case of overdose, get medical help or contact a Poison Control Center right away. (1-800-222-1222)

Directions

1. adults and children 12 years of age and over: take one tablet 30 minutes before going to bed; take once daily or as directed by a doctor
2. children under 12 years of age: do not use

Other information

1. store at 20-25°C (68-77°F)
2. keep carton. It contains important information.

Inactive ingredients

anhydrous dibasic calcium phosphate, dibasic calcium phosphate dihydrate, FD&C blue no. 1 aluminum lake, magnesium stearate, microcrystalline cellulose, sodium starch glycolate

Questions or comments?

1-800-719-9260

Principal Display Panel

CVS™

actual size

SLEEP-AID

Doxylamine Succinate Tablets, 25 mg

Nighttime Sleep-Aid

Compare to Unisom® SleepTabs® active ingredient

Helps to reduce difficulty in falling asleep

96 TABLETS

(ONE TABLET PER DOSE)